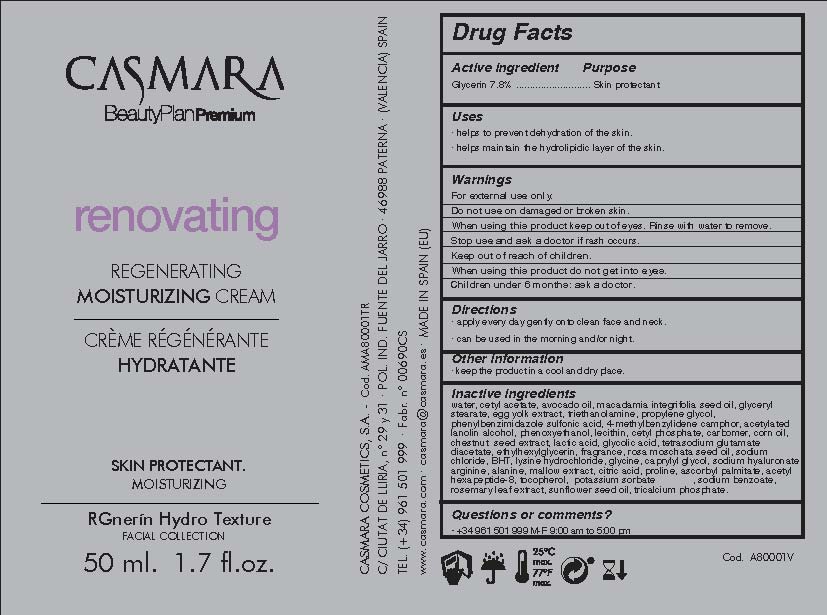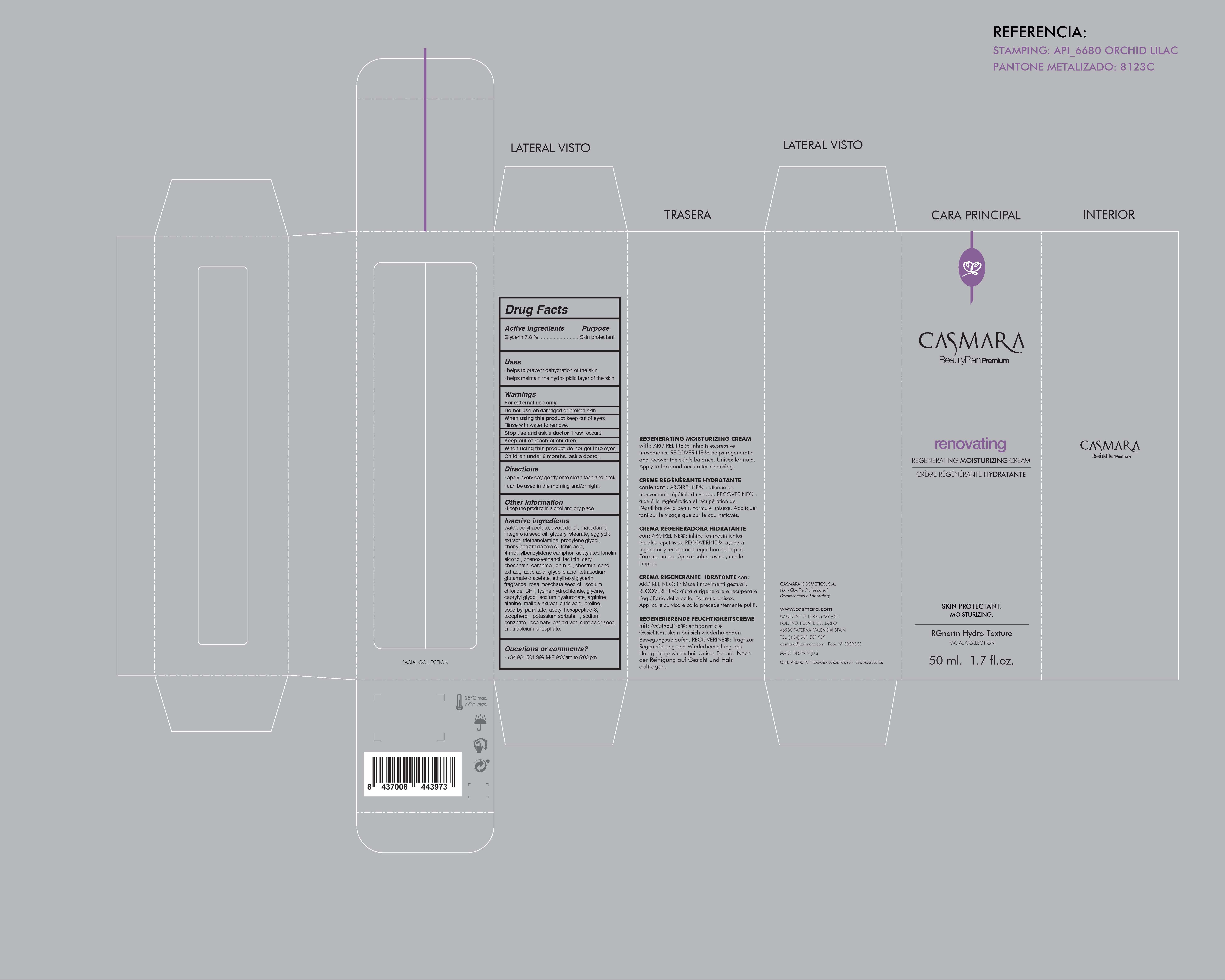 DRUG LABEL: Renovating Regenerating Moisturizing Cream
NDC: 20151-086 | Form: CREAM
Manufacturer: Casmara Cosmetics, SA
Category: otc | Type: HUMAN OTC DRUG LABEL
Date: 20170223

ACTIVE INGREDIENTS: GLYCERIN 7.8 mg/1 mL
INACTIVE INGREDIENTS: SPANISH CHESTNUT 0.4 mg/1 mL; ROSA MOSCHATA OIL 0.062 mg/1 mL; SODIUM CHLORIDE 0.03 mg/1 mL; GLYCOLIC ACID 0.21 mg/1 mL; CAPRYLYL GLYCOL 0.02 mg/1 mL; LYSINE HYDROCHLORIDE 0.02 mg/1 mL; GLYCINE 0.02 mg/1 mL; ASCORBYL PALMITATE 0.0023 mg/1 mL; SODIUM BENZOATE 0.0015 mg/1 mL; ROSEMARY 0.0012 mg/1 mL; CETYL PHOSPHATE 0.875 mg/1 mL; ETHYLHEXYLGLYCERIN 0.101 mg/1 mL; WATER 61.36 mg/1 mL; PHENOXYETHANOL 0.93 mg/1 mL; TETRASODIUM GLUTAMATE DIACETATE 0.103 mg/1 mL; TOCOPHEROL 0.002 mg/1 mL; PERFLUNAFENE 0.1 mg/1 mL; POTASSIUM SORBATE 0.0015 mg/1 mL; TROLAMINE 1.7 mg/1 mL; DIPROPYLENE GLYCOL 1.5 mg/1 mL; LECITHIN, SOYBEAN 0.875 mg/1 mL; TRICALCIUM PHOSPHATE 0.0001 mg/1 mL; ARGININE 0.01 mg/1 mL; HYALURONATE SODIUM 0.1 mg/1 mL; CITRIC ACID MONOHYDRATE 0.007 mg/1 mL; PROLINE 0.005 mg/1 mL; CETYL ACETATE 7.83 mg/1 mL; AVOCADO OIL 4 mg/1 mL; MACADAMIA OIL 3.99 mg/1 mL; ACETYLATED LANOLIN ALCOHOLS 1.17 mg/1 mL; CARBOXYPOLYMETHYLENE 0.5 mg/1 mL; ALANINE 0.01 mg/1 mL; MALVA SYLVESTRIS LEAF 0.009 mg/1 mL; ACETYL HEXAPEPTIDE-8 0.002 mg/1 mL; CORN OIL 0.4375 mg/1 mL; SUNFLOWER OIL 0.0012 mg/1 mL; LACTIC ACID 0.27 mg/1 mL; GLYCERYL STEARATE SE 2.8 mg/1 mL; EGG YOLK 2.8 mg/1 mL; BUTYLATED HYDROXYTOLUENE 0.022 mg/1 mL

Renovating Regenerating Moisturizing Cream

WARNINGS

For external use only.

Do not use on damaged or broken skin.

When using this product keep our of the eyes. Rinse with water to remove.

Stop use and ask a doctor if rash occurs.

Keep out of reach of children.

Whhen using this product do not get into eyes.

Children under 6 months: as a doctor.

Stop use and ask a doctor if rash occurs

Children under 6 months: ask a doctor

. keep out of reach of children

Questions or comments? + 34 961 501 099 M-F 9:00 am to 5:00 pm

OTHER SAFETY INFORMATION

. keep the product in a cool and dry place

Directions

. apply every day gently onto clean face and neck

. can be used in the morning and/or night

DOSAGE AND ADMINISTRATION

. apply every day gently onto clean dace and neck

. can be used in the morning and/or night

Uses

. helps to prevent dehydration of the skin.

. helps maintain the hydrolipidic layer of the skin

INACTIVE INGREDIENT

Water, Cetyl acetate, Avocado oil, Macadamia integrifolia seed oil, Glyceryl stearate, Egg yolk extract, Triethanolamine, Propylene glycol, Phenylbenzimidazole sulfonic acid, 4-methylbenzylidene camphor, Acetylated lanolin alcohol, Phenoxyethanol, Lecithin, Cetyl phosphate, Carbomer, Corn oil, Chestnut seed extract, Lactic acid, Glycolic acid, Tetrasodium glutamate diacetate, Ethylhexylglycerin, Fragrance, Rosa moschata seed oil, Sodium chloride, BHT, Lysine hydrochloride, Glycine, Caprylyl glycol, Sodium hyaluronate, Arginine, Alanine, Mallow extract, Citric acid, Proline, Ascorbyl palmitate, Acetyl hexapeptide-8, Tocopherol,Potassium sorbate, sodium benzoate, Rosemary leaf extract, Sunflower seed oil, Tricalcium phosphate

PURPOSE

. helps to prevent dehydration of the skin

. helps maintain the hydrolipidic layer of the skin

Active Ingredients

Glycerin 7.80%........................... Skin Protectant

PACKAGE LABEL

Renovating

Regenerating Moisturizing Cream

Skin Protectant

Moisturizing

RGnerin Hydro Texture

Facial Collection